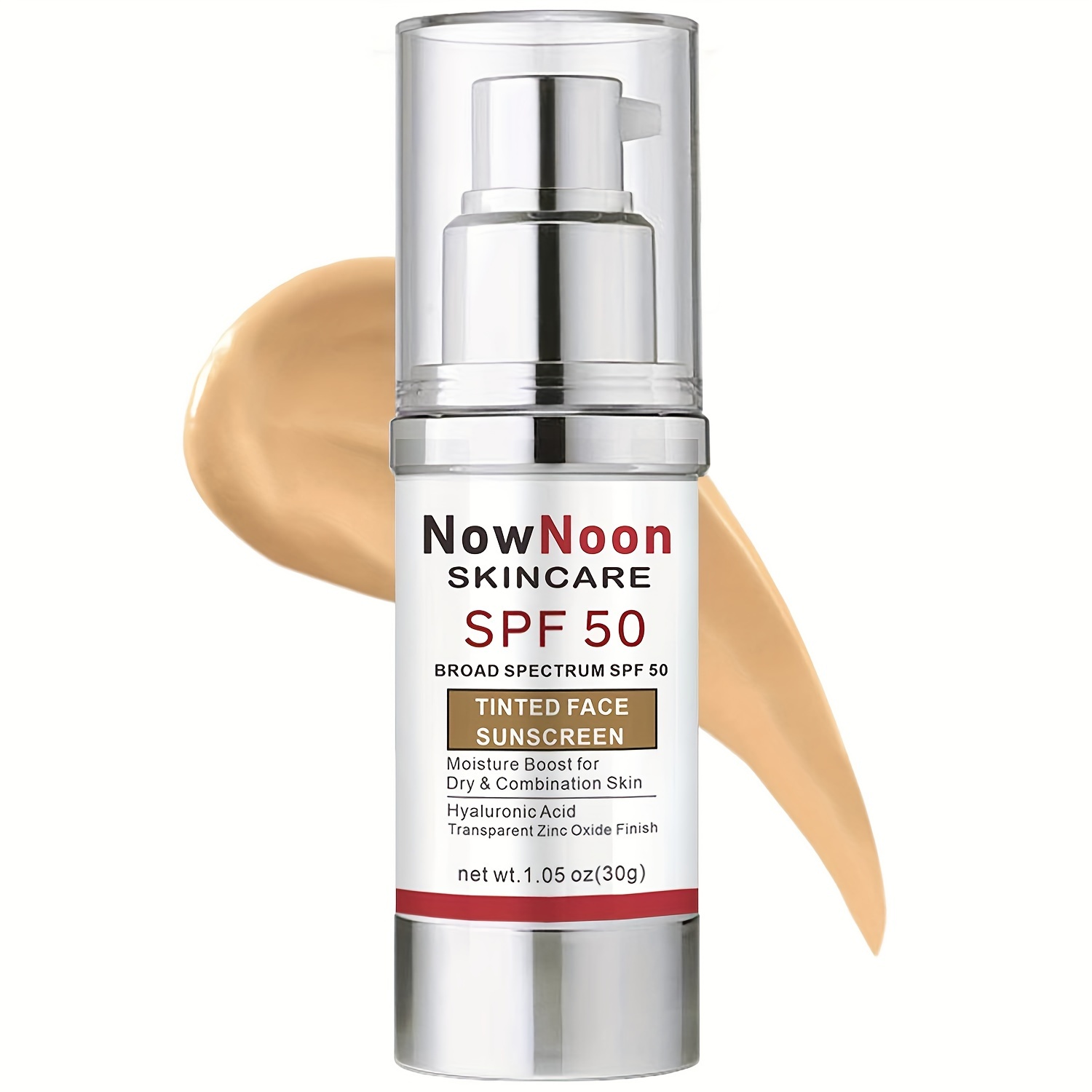 DRUG LABEL: NowNoon SKINCARE SPF 50 BROAD SPECTRUM SPF 50 TINTED FACE SUNSCREEN Cream
NDC: 84037-0076 | Form: CREAM
Manufacturer: Guangzhou Zhicunxiu Cosmetics Co., Ltd
Category: otc | Type: HUMAN OTC DRUG LABEL
Date: 20240427

ACTIVE INGREDIENTS: TITANIUM DIOXIDE 45 mg/1 g
INACTIVE INGREDIENTS: WATER; GLYCERIN; PROPYLPARABEN; OLEA EUROPAEA FRUIT VOLATILE OIL; PEG-20 HYDROGENATED LANOLIN; DIAZOLIDINYL UREA; CETYL ALCOHOL; ISOPROPYL PALMITATE; XANTHAN GUM; MINERAL OIL; GLYCERYL STEARATE/PEG-75 STEARATE; POTASSIUM LAURYL PHOSPHATE; METHYLPARABEN

NowNoon SKINCARE SPF 50 BROAD SPECTRUM SPF 50 TINTED FACE SUNSCREEN Cream

Active ingredients

Titanium Dioxide 4.5%

Purpose

Sunscreen

Uses

- Prevents sunburn, Hydrates, Moisturizes and repairs skin with anti-aging properties. Suitable for all skin types.
- If used as directed with other sun protection measures (see Directions), decreases the risk of skin cancer and early skin aging caused by the sun

Warnings

For external use only
Do not use on damaged or broken skin
When using this product keep out of eyes.
rinse with water to remove
Stop use and ask doctor if rash occurs
Keep out of reach of children

Direction

- Apply every morning or 15 min before sun exposure. For dry skin, apply after a layer of moisturizer. Reapply:
- after 80 minutes of swimming or sweating
- immediately after towel drying
- at least every 2 hours
- Sun protection measures. Use a broad spectrum sunscreen with an SPF value of 50 or higher
- limit time in the sun, especially from 10 am -2 pm
- wear long-sleeve shirts, pants, hats and sunglasses
- Children under 6 months of age: ask a doctor

Other information

Store at or below 77℉. Do not use if seal is broken

Inactive ingredients

Aqua, Glycerin, Cetearyl Alcohol, Isopropyl Palmitate, Mineral Oil, Potassium Lauryl Phosphate, Olea Europaea (Olive) Fruit Oil, Glyceryl Stearate, Hydrogenated Lanolin, Methylparaben, Xanthan Gum, CI 77492, Propylparaben, Fragrance, Triethanolamine, Diazolidinyl Urea, CI 77491, CI 77499

KEEP OUT OF REACH OF CHILDREN SECTION